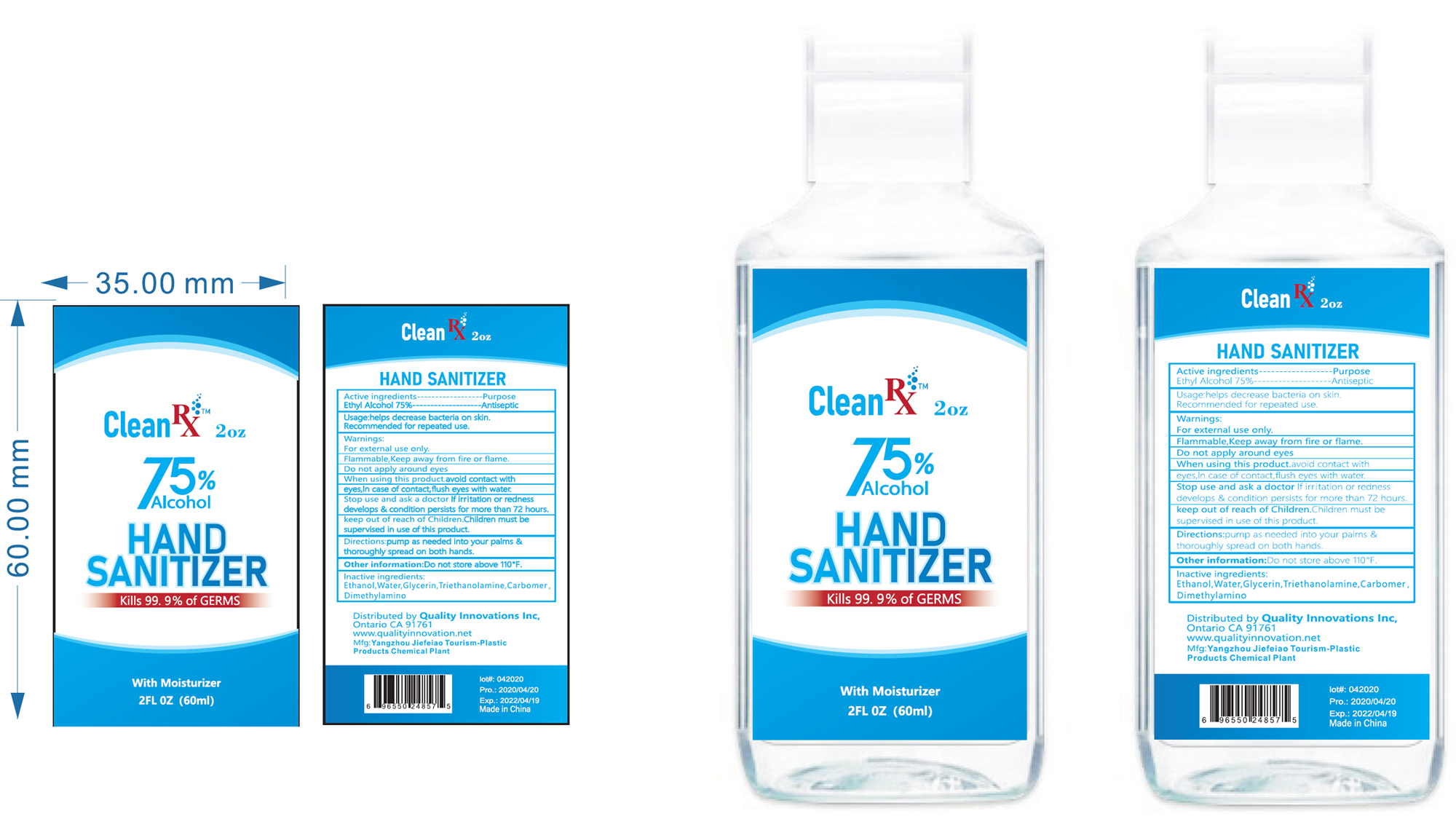 DRUG LABEL: Hand Sanitizer
NDC: 74235-001 | Form: GEL
Manufacturer: Quality Innovations Inc.
Category: otc | Type: HUMAN OTC DRUG LABEL
Date: 20200728

ACTIVE INGREDIENTS: ALCOHOL 75 mL/100 mL
INACTIVE INGREDIENTS: CARBOMER HOMOPOLYMER, UNSPECIFIED TYPE; TROLAMINE; WATER; DIMETHYLAMINE; GLYCERIN

Hand Sanitizer Gel

ACTIVE INGREDIENT

Alcohol 75% v/v. Purpose: Antiseptic

PURPOSE

Antiseptic, Hand Sanitizer

INDICATIONS AND USAGE

Help decrease bacteria on skin.

Recommended for repeated use

WARNINGS

For external use only

Flammable, keep away from fire or flame

Do not apply around eyes.

When using this product, avoid contact with eyes. In case of contact, flush eyes with water.

Stop use and ask a doctor if irritation or redness develops & condition persists for more than 72 hours.

KEEP OUT OF REACH OF CHILDREN

Keep our of reach of Children. Children must be supervised in use of this product.

DOSAGE AND ADMINISTRATION

Pump as needed into your palms & thoroughly spread on both hands.

OTHER SAFETY INFORMATION

Do not store above 110F

INACTIVE INGREDIENT

Water, Glycerin, Triethanolamine, Carbomer, Dimethylamino

Package Label - Principal Display Panel

60 mL NDC: 74235-001-01